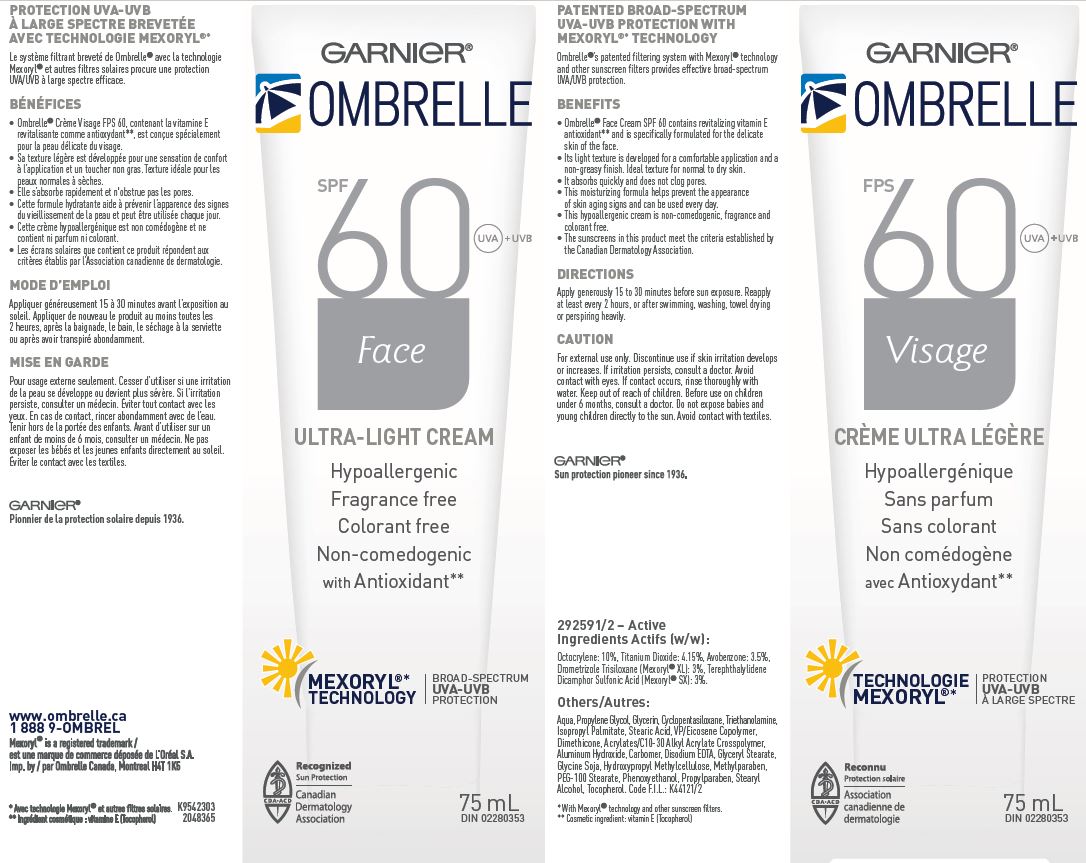 DRUG LABEL: Garnier Ombrelle SPF 60 Face Ultra Light
NDC: 49967-813 | Form: LOTION
Manufacturer: L'Oreal USA Products Inc
Category: otc | Type: HUMAN OTC DRUG LABEL
Date: 20260107

ACTIVE INGREDIENTS: OCTOCRYLENE 100 mg/1 mL; TITANIUM DIOXIDE 41.5 mg/1 mL; AVOBENZONE 35 mg/1 mL; DROMETRIZOLE TRISILOXANE 30 mg/1 mL; ECAMSULE 30 mg/1 mL
INACTIVE INGREDIENTS: water; PROPYLENE GLYCOL; GLYCERIN; CYCLOMETHICONE 5; TROLAMINE; ISOPROPYL PALMITATE; STEARIC ACID; VINYLPYRROLIDONE/EICOSENE COPOLYMER; DIMETHICONE; ALUMINUM HYDROXIDE; CARBOXYPOLYMETHYLENE; EDETATE DISODIUM; GLYCERYL MONOSTEARATE; SOYBEAN OIL; HYPROMELLOSE, UNSPECIFIED; METHYLPARABEN; PEG-100 STEARATE; PHENOXYETHANOL; PROPYLPARABEN; STEARYL ALCOHOL; TOCOPHEROL; CARBOMER INTERPOLYMER TYPE A (ALLYL SUCROSE CROSSLINKED)

Drug Facts

Active ingredients

Octocrylene 10%

Titanium Dioxide 4.15%

Avobenzone 3.5%

Drometrizole Trisiloxane 3%

Terephthalylidene Dicamphor Sulfonic Acid 3%

Caution

For external use only. Discontinue use if skin irratation develops or increases. If irritation persists, consult a doctor. Avoid contact with eyes. If contact occurs, rinse thoroughly with water. Keep out of reach of children. Before use on children under 6 months, consult a doctor. Do not expose babies and young children directly to the sun. Avoid contact with textiles.

Directions

Apply generously 15 to 30 minutes before sun exposure. Reapply at least every 2 hours or after swimming, washing, towel drying or perspiring heavily.

Others

Aqua, Propylene Glycol, Glycerin, Cyclopentasiloxane, Triethanolamine, Isopropyl Palmitate, Stearic Acid, VP/Eicosene Copolymer, Dimethicone, Acrylates/C10-30 Alkyl Acrylate Crosspolymer, Aluminum Hydroxide, Carbomer, Disodium EDTA, Glyceryl Stearate, Glycine Soja, Hydroxypropyl Methylcellulose, Methylparaben, PEG-100 Stearate, Phenoxyethanol, Propylparaben, Stearyl alcohol, Tocopherol